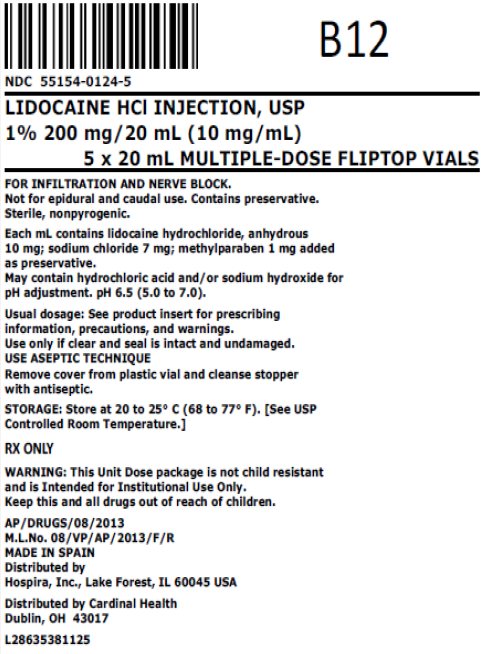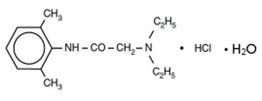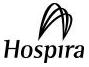 DRUG LABEL: Lidocaine Hydrochloride
NDC: 55154-0124 | Form: INJECTION, SOLUTION
Manufacturer: Cardinal Health 107, LLC
Category: prescription | Type: HUMAN PRESCRIPTION DRUG LABEL
Date: 20260216

ACTIVE INGREDIENTS: LIDOCAINE HYDROCHLORIDE 10 mg/1 mL
INACTIVE INGREDIENTS: WATER; METHYLPARABEN 1 mg/1 mL; SODIUM CHLORIDE 7 mg/1 mL

HIGHLIGHTS OF PRESCRIBING INFORMATION

These highlights do not include all the information needed to use LIDOCAINE HYDROCHLORIDE INJECTION, USP safely and effectively. See full prescribing information for LIDOCAINE HYDROCHLORIDE INJECTION, USP.
LIDOCAINE HYDROCHLORIDE INJECTION, USP, aqueous solutions for infiltration and nerve block
Initial U.S. Approval: 1948

1 INDICATIONS AND USAGE

Lidocaine Hydrochloride Injection contains lidocaine, an amide local anesthetic. Lidocaine Hydrochloride Injection is indicated in adult and pediatric patients for the production of local or regional anesthesia or analgesia for surgery, dental, and oral surgery procedures, diagnostic and therapeutic procedures, and for obstetrical procedures. For each type of block indicated to produce local or regional anesthesia or analgesia, specific concentrations and presentations are recommended. (1, 2.2)

2 DOSAGE AND ADMINISTRATION

See Full Prescribing Information for recommended dosages and administration information for adult and pediatric patients. (2)

3 DOSAGE FORMS AND STRENGTHS

- Lidocaine Hydrochloride Injection, single-dose vials: 0.5%, 1% (3)
- Lidocaine Hydrochloride Injection, single-dose ampuls: 1%, 1.5%, 2% (3)
- Lidocaine Hydrochloride Injection, multiple-dose vials: 0.5%, 1%, 2% (3)

4 CONTRAINDICATIONS

- Known hypersensitivity to any local anesthetic agent of the amide-type or to other components of Lidocaine Hydrochloride Injection. (4)

5 WARNINGS AND PRECAUTIONS

- Dose-Related Toxicity: Monitor cardiovascular and respiratory vital signs and patient’s state of consciousness after injection of Lidocaine Hydrochloride Injection. (5.1)
- Methemoglobinemia: Cases of methemoglobinemia have been reported in association with local anesthetics use. See full prescribing information for more details on managing these risks. (5.2)
- Chondrolysis with Intra-Articular Infusion: Avoid intra-articular infusions as there have been post-marketing reports of chondrolysis in patients receiving such infusion. (5.4)
- Risk of Systemic Toxicities with Unintended Intravascular or Intrathecal Injection: Unintended intravascular or intrathecal injection may be associated with systemic toxicities, including CNS or cardiorespiratory depression and coma, progression ultimately to respiratory arrest. Aspirate for blood or cerebrospinal fluid (where applicable) prior to each dose and consider using a test dose of a lidocaine solution containing epinephrine. (5.7)

6 ADVERSE REACTIONS

Most common adverse reactions are as follows:

- Central Nervous System: Lightheadedness, nervousness, apprehension, euphoria, confusion, dizziness, drowsiness, tinnitus, blurred or double vision, vomiting, sensations of heat, cold or numbness, twitching, tremors, convulsions, unconsciousness, respiratory depression and arrest. (6)
- Cardiovascular System: Bradycardia, hypotension, and cardiovascular collapse. (6)
- Allergic: Cutaneous lesions, urticaria, edema or anaphylactoid reactions. (6)
- Neurologic: Positional headaches, hypotension and backache. (6)
- Hematologic: Methemoglobinemia. (6)

To report SUSPECTED ADVERSE REACTIONS, contact Pfizer Inc. at 1‑800‑438‑1985 or FDA at 1-800-FDA-1088 or www.fda.gov/medwatch.

7 DRUG INTERACTIONS

- Local Anesthetics: The toxic effects of local anesthetics are additive. Monitor for neurologic and cardiovascular effects when additional local anesthetics are administered. (7.1)
- Monoamine Oxidase Inhibitors and Tricyclic Antidepressants: Administration of lidocaine solutions containing epinephrine to patients receiving monoamine oxidase inhibitors or tricyclic antidepressants may produce severe, prolonged hypertension. Concurrent use of these agents should generally be avoided. (5.5, 7.2)
- Ergot-type Oxytocic drugs: Concurrent administration of lidocaine solutions containing epinephrine and ergot-type oxytocic drugs may cause severe, persistent hypertension or cerebrovascular accidents. (5.5, 7.3)
- Nonselective Beta-Adrenergic Antagonists: Administration of lidocaine solutions containing epinephrine in patients receiving nonselective beta-adrenergic antagonist may cause severe hypertension and bradycardia. Concurrent use of these agents should generally be avoided. (5.5, 7.4)
- Drugs Associated with Methemoglobinemia: Patients are at increased risk of developing methemoglobinemia when concurrently exposed to nitrates, nitrites, local anesthetics, antineoplastic agents, antibiotics, antimalarials, anticonvulsants and other drugs. (7.5)
- Potent Inhalation Anesthetics: Serious dose-related cardiac arrhythmias may occur if lidocaine solutions containing epinephrine are used in patients during or following the administration of potent inhalation anesthetics. (5.11, 7.6)

8 USE IN SPECIFIC POPULATIONS

- Geriatric Use: Elderly patients should be given reduced doses commensurate with their age and physical condition. (8.5)
- Hepatic Impairment: Consider reduced dosing and increased monitoring for local anesthetic systemic toxicity in patients with hepatic impairment. (8.6)

FULL PRESCRIBING INFORMATION

1 INDICATIONS AND USAGE

Lidocaine Hydrochloride Injection is indicated in adult and pediatric patients for the production of local or regional anesthesia or analgesia for surgery, dental, and oral surgery procedures, diagnostic and therapeutic procedures, and for obstetrical procedures. Specific concentrations and presentations of Lidocaine Hydrochloride Injection are recommended for each type of block indicated to produce local or regional anesthesia or analgesia [see Dosage and Administration (2.2)].

2 DOSAGE AND ADMINISTRATION

2.1 Important Dosage and Administration Information

- Lidocaine Hydrochloride Injection is not recommended for intrathecal use.
- Avoid use of Lidocaine Hydrochloride Injection solutions containing antimicrobial preservatives (i.e., multiple-dose vials) for epidural or caudal anesthesia [see Warnings and Precautions (5.3)].
- Discard unused portions of solution not containing preservatives, i.e., those supplied in single-dose vials, following initial use.
- Visually inspect this product for particulate matter and discoloration prior to administration whenever solution and container permit. Lidocaine Hydrochloride Injection is a clear solution. Do not administer solutions which are discolored or contain particulate matter.
- Mixing or the prior or intercurrent use of any other local anesthetic with Lidocaine Hydrochloride Injection is not recommended because of insufficient data on the clinical use of such mixtures.

Administration Precautions

- Lidocaine Hydrochloride Injection is to be administered in carefully adjusted dosages by or under the supervision of experienced clinicians who are well versed in the diagnosis and management of dose‑related toxicity and other acute emergencies which might arise from the block to be employed.
- Use Lidocaine Hydrochloride Injection only if the following are immediately available: oxygen, cardiopulmonary resuscitative equipment and drugs, and the personnel resources needed for proper management of toxic reactions and related emergencies [see Warnings and Precautions (5.1), Adverse Reactions (6), Overdosage (10)].
- The toxic effects of local anesthetics are additive. Monitor for neurologic and cardiovascular effects related to local anesthetic systemic toxicity when additional local anesthetics are administered with Lidocaine Hydrochloride Injection [see Warnings and Precautions (5.1), Drug Interactions (7.1), Overdosage (10)].
- Aspirate for blood or cerebrospinal fluid (where applicable) prior to injecting Lidocaine Hydrochloride Injection, both the initial dose and all subsequent doses, to avoid intravascular or intrathecal injection. However, a negative aspiration for blood or cerebrospinal fluid does not ensure against an intravascular or intrathecal injection [see Warnings and Precautions (5.7)].
- Avoid rapid injection of a large volume of Lidocaine Hydrochloride Injection and use fractional (incremental) doses when feasible.
- During major regional nerve blocks, such as those of the brachial plexus or lower extremity, the patient should have an indwelling intravenous catheter to assure adequate intravenous access. The lowest dosage of Lidocaine Hydrochloride Injection that results in effective anesthesia should be used to avoid high plasma levels and serious adverse reactions.
- Perform careful and constant monitoring of cardiovascular and respiratory (adequacy of oxygenation and ventilation) vital signs and the patient’s level of consciousness after each local anesthetic injection.
- Use lidocaine solutions containing epinephrine in carefully restricted quantities in areas of the body supplied by end arteries or having otherwise compromised blood supply such as digits, nose, external ear, or penis [see Warnings and Precautions (5.10)].

2.2 Recommended Concentrations and Dosages of Lidocaine Hydrochloride Injection in Adults

The dosage of Lidocaine Hydrochloride Injection administered varies with the anesthetic procedure, the area to be anesthetized, the vascularity of the tissues, the number of neuronal segments to be blocked, the depth of anesthesia and degree of muscle relaxation required, the duration of anesthesia desired, individual tolerance, and the physical condition of the patient. Administer the smallest dosage and concentration required to produce the desired result.

The types of block and recommended Lidocaine Hydrochloride Injection concentrations are shown in Table 1. The dosages suggested in this table are for normal healthy adults and refer to the use of epinephrine-free solutions. Consider administration of solutions containing epinephrine when large volumes are required.

Table 1: Recommended Dosages in Adults

Procedure | Lidocaine Hydrochloride Injection; (without Epinephrine)
Procedure | Conc. (%) | Vol. (mL) | Total Dose (mg)
Infiltration
Percutaneous | 0.5 or 1 | 1 to 60 | 5 to 300
Intravenous regional | 0.5 | 10 to 60 | 50 to 300 [Dose should not exceed 4 mg/kg.]
Peripheral Nerve Blocks, e.g.,
Brachial | 1.5 | 15 to 20 | 225 to 300
Dental | 2 | 1 to 5 | 20 to 100
Intercostal | 1 | 3 | 30
Paravertebral | 1 | 3 to 5 | 30 to 50
Pudendal (each side) | 1 | 10 | 100
Paracervical
Obstetrical analgesia (each side) | 1 | 10 | 100
Sympathetic Nerve Blocks, e.g.,
Cervical (stellate ganglion) | 1 | 5 | 50
Lumbar | 1 | 5 to 10 | 50 to 100
Central Neural Blocks
Epidural [Dose determined by number of dermatomes to be anesthetized (2 to 3 mL/dermatome).]
Thoracic | 1 | 20 to 30 | 200 to 300
Lumbar
Analgesia | 1 | 25 to 30 | 250 to 300
Anesthesia | 1.5 | 15 to 20 | 225 to 300
 | 2 | 10 to 15 | 200 to 300
Caudal
Obstetrical analgesia | 1 | 20 to 30 | 200 to 300
Surgical anesthesia | 1.5 | 15 to 20 | 225 to 300

The above suggested concentrations and volumes serve only as a guide. Other volumes and concentrations may be used provided the total maximum recommended dose is not exceeded [see Dosage and Administration (2.5)].

These recommended doses serve only as a guide to the amount of local anesthetic required for most indicated procedures. The actual volumes and concentrations to be used depend on a number of factors such as type and extent of surgical procedure, depth of anesthesia and degree of muscular relaxation required, duration of anesthesia required, and the physical condition of the patient. In all cases, the lowest concentration and smallest dose that will produce the desired result should be given. The maximum dosage limit within the recommended dosage range must be individualized in each case after evaluating the size and physical status of the patient, as well as the anticipated rate of systemic absorption from a particular injection site.

2.3 Use in Epidural Anesthesia

During the administration of epidural anesthesia, it is recommended that a test dose of a lidocaine solution containing epinephrine be administered initially and the effects monitored before the full dose is given. When using a “continuous” catheter technique, test doses should be given prior to both the initial and all supplemental doses, because a catheter in the epidural space can migrate into a blood vessel or through the dura [see Dosage and Administration (2.4)].

During epidural administration, administer Lidocaine Hydrochloride Injection 1% (10 mg/mL), 1.5% (15 mg/mL, and 2% (20 mg/mL) solutions in incremental doses of 3 mL to 5 mL with sufficient time between doses to detect toxic manifestations of unintentional intravascular or intrathecal injection. Administer injections slowly, with frequent aspirations before and during the injection to avoid intravascular injection. Perform syringe aspirations before and during each supplemental injection in continuous (intermittent) catheter techniques. Repeat doses of Lidocaine Hydrochloride Injection should be preceded by a test dose containing epinephrine if not clinically contraindicated. Use only the single-dose vials for caudal or epidural anesthesia; avoid use of the multiple-dose vials for these procedures, which contain a preservative [see Dosage and Administration (2.1, 2.4), Warnings and Precautions (5.7)].

2.4 Test Dose for Epidural Blocks

In the event of the known injection of a large volume of local anesthetic solution into the subarachnoid space, after suitable resuscitation and if the catheter is in place, consider attempting the recovery of drug by draining a moderate amount of cerebrospinal fluid (such as 10 mL) through the epidural catheter.

A lidocaine solution containing epinephrine is recommended for use as a test dose prior to caudal and lumbar epidural blocks when clinical conditions permit. This test dose may serve as a warning of unintended intravascular or intrathecal injection. Closely monitor for early clinical signs of toxicity following each test dose [see Warnings and Precautions (5.7)]. Allot adequate time for onset of spinal block to detect possible intrathecal injection. An intravascular or intrathecal injection is still possible even if results of the test dose are negative. The test dose itself may produce a systemic toxic reaction, high spinal, or cardiovascular effects from the epinephrine [see Warnings and Precautions (5.1), Overdosage (10)].

2.5 Intravenous Regional Anesthesia (Bier Block)

For intravenous regional anesthesia, use only the 50 mL single-dose vial containing Lidocaine Hydrochloride Injection 0.5%. Lidocaine solutions containing epinephrine or other vasoconstrictors should not be used for this technique. Proper use of the double tourniquet technique is essential in the performance of intravenous regional anesthesia.

For intravenous regional anesthesia, the dose administered should not exceed 4 mg/kg in adults.

2.6 Maximum Recommended Dosage

NOTE: The products accompanying this insert do not contain epinephrine.

Adults

The maximum individual dose of lidocaine hydrochloride should not exceed 4.5 mg/kg of body weight, and in general it is recommended that the maximum total dose does not exceed 300 mg. For continuous epidural or caudal anesthesia, the maximum recommended dosage should not be administered at intervals of less than 90 minutes. When continuous lumbar or caudal epidural anesthesia is used for non-obstetrical procedures, a higher total dose may be administered if required to produce adequate anesthesia.

The maximum recommended dose per 90 minute period of lidocaine hydrochloride for paracervical block in obstetrical patients and non-obstetrical patients is 200 mg total. One half of the total dose is usually administered to each side. Inject slowly, five minutes between sides [see Pregnancy (8.1)].

Pediatric Patients

A maximum dose of Lidocaine Hydrochloride Injection for children varies based on age and weight. For children over 3 years of age with a normal lean body mass and normal body development, the maximum dose is determined by the child’s age and weight. For example, in a child of 5 years weighing approximately 23 kg, the dose of lidocaine hydrochloride should not exceed approximately 75 mg to 100 mg (3.3 mg/kg to 4.4 mg/kg). The use of dilute solutions (i.e., 0.25% to 0.5%) and total dosages not to exceed 3 mg/kg are recommended for induction of intravenous regional anesthesia in children.

The lowest effective concentration and lowest effective dose should be used. Dilution of available concentrations with 0.9% sodium chloride injection may be required to obtain the required final concentration.

3 DOSAGE FORMS AND STRENGTHS

Lidocaine Hydrochloride Injection, USP is a clear solution available as:

- 0.5% (250 mg per 50 mL) (5 mg per mL), 50 mL single-dose teartop vials
- 1% (20 mg per 2 mL) (10 mg per mL), 2 mL single-dose ampuls
- 1% (50 mg per 5 mL) (10 mg per mL), 5 mL single-dose ampuls
- 1% (300 mg per 30 mL) (10 mg per mL), 30 mL single-dose teartop vials
- 1.5% (300 mg per 20 mL) (15 mg per mL), 20 mL single-dose ampuls
- 2% (40 mg per 2 mL) (20 mg per mL), 2 mL single-dose ampuls
- 2% (200 mg per 10 mL) (20 mg per mL), 10 mL single-dose ampuls
- 0.5% (250 mg per 50 mL) (5 mg per mL), 50 mL multiple-dose fliptop vials
- 1% (200 mg per 20 mL) (10 mg per mL), 20 mL multiple-dose fliptop vials
- 1% (500 mg per 50 mL) (10 mg per mL), 50 mL multiple-dose fliptop vials
- 2% (400 mg per 20 mL) (20 mg per mL), 20 mL multiple-dose fliptop vials
- 2% (1000 mg per 50 mL) (20 mg per mL), 50 mL multiple-dose fliptop vials

4 CONTRAINDICATIONS

Lidocaine Hydrochloride Injection is contraindicated in patients with a known hypersensitivity to lidocaine or to any local anesthetics of the amide-type or to other components of Lidocaine Hydrochloride Injection.

5 WARNINGS AND PRECAUTIONS

5.1 Dose-Related Toxicity

The safety and effectiveness of Lidocaine Hydrochloride Injection depends on proper dosage, correct technique, adequate precautions, and readiness for emergencies. Careful and constant monitoring of cardiovascular and respiratory (adequacy of ventilation) vital signs and the patient’s state of consciousness should be performed after injection of Lidocaine Hydrochloride Injection solutions.

Possible early warning signs of central nervous system (CNS) toxicity are restlessness, anxiety, incoherent speech, lightheadedness, numbness and tingling of the mouth and lips, metallic taste, tinnitus, dizziness, blurred vision, tremors, twitching, CNS depression, or drowsiness. Delay in proper management of dose-related toxicity, underventilation from any cause and/or altered sensitivity may lead to the development of acidosis, cardiac arrest and, possibly, death.

During major regional nerve blocks, such as those of the brachial plexus or lower extremity, the patient should have an indwelling intravenous catheter to assure adequate intravenous access. Use the lowest dosage of Lidocaine Hydrochloride Injection that results in effective anesthesia to avoid high plasma levels and serious adverse effects. Avoid rapid injection of a large volume of Lidocaine Hydrochloride Injection solution and administer fractional (incremental) doses when feasible.

Injection of repeated doses of Lidocaine Hydrochloride Injection may cause significant increases in plasma levels with each repeated dose due to slow accumulation of the drug or its metabolites, or to slow metabolic degradation. Tolerance to elevated blood levels varies with the status of the patient. Debilitated, elderly patients and acutely ill patients should be given reduced doses commensurate with their age and physical status.

5.2 Methemoglobinemia

Cases of methemoglobinemia have been reported in association with local anesthetic use. Although all patients are at risk for methemoglobinemia, patients with glucose-6-phosphate dehydrogenase deficiency, congenital or idiopathic methemoglobinemia, cardiac or pulmonary compromise, infants under 6 months of age, and concurrent exposure to oxidizing agents or their metabolites are more susceptible to developing clinical manifestations of the condition [see Drug Interactions (7.5)]. If local anesthetics must be used in these patients, close monitoring for symptoms and signs of methemoglobinemia is recommended.

Signs of methemoglobinemia may occur immediately or may be delayed some hours after exposure and are characterized by a cyanotic skin discoloration and abnormal coloration of the blood. Methemoglobin levels may continue to rise; therefore, immediate treatment is required to avert more serious central nervous system and cardiovascular adverse effects, including seizures, coma, arrhythmias, and death. Discontinue Lidocaine Hydrochloride Injection and any other oxidizing agents. Depending on the severity of the symptoms, patients may respond to supportive care, i.e., oxygen therapy, hydration. More severe symptoms may require treatment with methylene blue, exchange transfusion, or hyperbaric oxygen.

5.3 Antimicrobial Preservatives in Multiple-Dose Vials

Avoid use of Lidocaine Hydrochloride Injection solutions containing antimicrobial preservatives (i.e., those supplied in multiple-dose vials) for epidural or caudal anesthesia because safety has not been established with such use.

5.4 Chondrolysis with Intra-Articular Infusion

Intra-articular infusions of local anesthetics following arthroscopic and other surgical procedures is an unapproved use, and there have been post-marketing reports of chondrolysis in patients receiving such infusions. The majority of reported cases of chondrolysis have involved the shoulder joint; cases of gleno‑humeral chondrolysis have been described in pediatric and adult patients following intra-articular infusions of local anesthetics with and without epinephrine for periods of 48 to 72 hours. There is insufficient information to determine whether shorter infusion periods are not associated with these findings. The time of onset of symptoms, such as joint pain, stiffness and loss of motion can be variable, but may begin as early as the 2nd month after surgery. Currently, there is no effective treatment for chondrolysis; patients who experienced chondrolysis have required additional diagnostic and therapeutic procedures and some required arthroplasty or shoulder replacement.

5.5 Risk of Adverse Reactions Due to Drug Interactions with Lidocaine Solutions Containing Epinephrine

Risk of Severe, Persistent Hypertension Due to Drug Interactions Between Lidocaine Solutions Containing Epinephrine and Monoamine Oxidase Inhibitors and Tricyclic Antidepressants

Administration of lidocaine solutions containing epinephrine in patients receiving monoamine oxidase inhibitors (MAOI), or tricyclic antidepressants may result in severe, prolonged hypertension. Concurrent use of these agents should generally be avoided. In situations when concurrent therapy is necessary, careful monitoring of the patient's hemodynamic status is essential [see Drug Interactions (7.2)].

Risk of Severe, Persistent Hypertension or Cerebrovascular Accidents Due to Drug Interactions Between Lidocaine Solutions Containing Epinephrine and Ergot-Type Oxytocic Drugs

Concurrent administration of lidocaine solutions containing epinephrine and ergot-type oxytocic drugs may cause severe, persistent hypertension or cerebrovascular accidents. Avoid use of lidocaine solutions containing epinephrine concomitantly with ergot-type oxytocic drugs [see Drug Interactions (7.3)].

Risk of Hypertension and Bradycardia Due to Drug Interactions Between Lidocaine Solutions Containing Epinephrine and Nonselective Beta-Adrenergic Antagonists

Administration of lidocaine solutions containing epinephrine in patients receiving nonselective beta-adrenergic antagonists may cause severe hypertension and bradycardia. Concurrent use of these agents should generally be avoided. In situations when concurrent therapy is necessary, careful monitoring of the patient's blood pressure and heart rate is essential [see Drug Interactions (7.4)].

5.6 Anaphylactic Reactions

Anaphylactic reactions may occur following administration of lidocaine hydrochloride [see Adverse Reactions (6)]. Lidocaine hydrochloride should be used with caution in persons with known drug sensitivities. Patients allergic to para-aminobenzoic acid derivatives (procaine, tetracaine, benzocaine, etc.) have not shown cross‑sensitivity to lidocaine hydrochloride.

5.7 Risk of Systemic Toxicities with Unintended Intravascular or Intrathecal Injection

Unintended intravascular or intrathecal injection of Lidocaine Hydrochloride Injection may be associated with systemic toxicities, including CNS or cardiorespiratory depression and coma, progressing ultimately to respiratory arrest. Unintentional intrathecal injection during the intended performance of caudal or lumbar epidural block or nerve blocks near the vertebral column has resulted in underventilation or apnea ("Total or High Spinal"). A high spinal has been characterized by paralysis of the legs, loss of consciousness, respiratory paralysis, and bradycardia [see Adverse Reactions (6)].

Aspirate for blood or cerebrospinal fluid (where applicable) before injecting Lidocaine Hydrochloride Injection, both the initial dose and all subsequent doses, to avoid intravascular or intrathecal injection. However, a negative aspiration for blood or cerebrospinal fluid does not ensure against an intravascular or intrathecal injection.

Use of Test Dose with Epidural Anesthesia

To serve as a warning of unintended intravascular or intrathecal injection, a lidocaine solution containing epinephrine may be used for a test dose prior to administration of the full dose in caudal and lumbar epidural blocks [see Dosage and Administration (2.4)]. An intravascular or intrathecal injection is still possible even if results of the test dose are negative.

Signs/symptoms of unintended intravascular or intrathecal injection of the test dose and monitoring recommendations are described below.

- Unintended intravascular injection: Likely to produce a transient “epinephrine response” within 45 seconds, consisting of an increase in heart rate and/or systolic blood pressure, circumoral pallor, palpitations, and nervousness in the unsedated patient. The sedated patient may exhibit only a pulse rate increase of 20 or more beats per minute for 15 or more seconds. Therefore, following the test dose, the heart rate should be monitored for increases. Patients on beta-blockers may not manifest changes in heart rate, but blood pressure monitoring can detect a transient rise in systolic blood pressure.
- Unintended intrathecal injection: Evidenced within a few minutes by signs of spinal block (e.g., decreased sensation of the buttocks, paresis of the legs, or, in the sedated patient, absent knee jerk).

The test dose itself may produce a systemic toxic reaction, high spinal or epinephrine-induced cardiovascular effects [see Overdosage (10)].

5.8 Risk of Toxicity in Patients with Hepatic Impairment

Because amide local anesthetics such as lidocaine are metabolized by the liver, consider reduced dosing and increased monitoring for lidocaine systemic toxicity in patients with moderate to severe hepatic impairment who are treated with Lidocaine Hydrochloride Injection, especially with repeat doses [see Use in Specific Populations (8.6)].

5.9 Risk of Use in Patients with Impaired Cardiovascular Function

Lidocaine Hydrochloride Injection should also be given in reduced doses in patients with impaired cardiovascular function since they may be less able to compensate for functional changes associated with the prolongation of A-V conduction produced by these drugs. Monitor patients closely for blood pressure, heart rate, and ECG changes.

5.10 Risk of Ischemic Injury or Necrosis in Body Areas with Limited Blood Supply

Use lidocaine solutions containing epinephrine in carefully restricted quantities in areas of the body supplied by end arteries or having otherwise compromised blood supply, such as digits, nose, external ear, or penis. Patients with peripheral vascular disease and those with hypertensive vascular disease may exhibit exaggerated vasoconstrictor response. Ischemic injury or necrosis may result.

5.11 Risk of Cardiac Arrhythmias with Concomitant Use of Potent Inhalation Anesthetics

Serious dose-related cardiac arrhythmias may occur if preparations containing a vasoconstrictor such as epinephrine are used in patients during or following the administration of potent inhalation anesthetics [see Drug Interactions (7.6)]. In deciding whether to concurrently use lidocaine solutions containing epinephrine with potent inhalation anesthetics in the same patient, the combined action of both agents upon the myocardium, the concentration and volume of vasoconstrictor used, and the time since injection, when applicable, should be taken into account.

5.12 Risk of Adverse Reactions with Use in the Head and Neck Area

Small doses of local anesthetics (e.g., Lidocaine Hydrochloride Injection) injected into the head and neck area, including retrobulbar, dental and stellate ganglion blocks, may produce adverse reactions similar to systemic toxicity seen with unintentional intravascular injections of larger doses. The injection procedures require the utmost care. Confusion, convulsions, respiratory depression and/or respiratory arrest, and cardiovascular stimulation or depression have been reported. These reactions may be due to intra-arterial injection of the local anesthetic with retrograde flow to the cerebral circulation. They may also be due to puncture of the dural sheath of the optic nerve during retrobulbar block with diffusion of any local anesthetic along the subdural space to the midbrain. Monitor circulation and respiration and constantly observe patients receiving Lidocaine Hydrochloride Injection blocks. Resuscitative equipment and drugs, and personnel for treating adverse reactions should be immediately available. Dosage recommendations should not be exceeded [see Dosage and Administration (2.2)].

5.13 Familial Malignant Hyperthermia

Many drugs used during the conduct of anesthesia are considered potential triggering agents for familial malignant hyperthermia. Since it is not known whether amide-type local anesthetics may trigger this reaction and since the need for supplemental general anesthesia cannot be predicted in advance, it is suggested that a standard protocol for the management of malignant hyperthermia should be available. Early unexplained signs of tachycardia, tachypnea, labile blood pressure and metabolic acidosis may precede temperature elevation. Successful outcome is dependent on early diagnosis, prompt discontinuance of the suspect triggering agent(s) and institution of treatment, including oxygen therapy, indicated supportive measures and dantrolene (consult dantrolene sodium intravenous package insert before using).

5.14 Risk of Respiratory Arrest with Use in Ophthalmic Surgery

Clinicians who perform retrobulbar blocks should be aware that there have been reports of respiratory arrest following local anesthetic injection. Prior to retrobulbar block (e.g., with Lidocaine Hydrochloride Injection), as with all other regional procedures, resuscitative equipment and drugs, and personnel to manage respiratory arrest or depression, convulsions, and cardiac stimulation or depression should be immediately available [see Warnings and Precautions (5.12)]. As with other anesthetic procedures, patients should be constantly monitored following ophthalmic blocks for signs of these adverse reactions, which may occur following relatively low total doses.

5.15 Risk of Inadvertent Trauma to Tongue, Lips, and Buccal Mucosa in Dental Applications

Because of the long duration of anesthesia, when Lidocaine Hydrochloride Injection is used for dental injections, warn patients about the possibility of inadvertent trauma to tongue, lips, and buccal mucosa and advise them not to chew solid foods until sensation returns [see Patient Counseling Information (17)].

5.16 Drug/Laboratory Test Interactions

The intramuscular injection of lidocaine hydrochloride may result in an increase in creatine phosphokinase levels. Thus, the use of this enzyme determination, without isoenzyme separation, as a diagnostic test for the presence of acute myocardial infarction may be compromised by the intramuscular injection of lidocaine hydrochloride.

6 ADVERSE REACTIONS

The following clinically significant adverse reactions have been reported and described in the Warnings and Precautions section of the labeling:

- Dose-Related Toxicity [see Warnings and Precautions (5.1)]
- Methemoglobinemia [see Warnings and Precautions (5.2)]
- Chondrolysis with Intra-Articular Infusion [see Warnings and Precautions (5.4)]
- Severe, Persistent Hypertension, Cerebrovascular Accidents, and Bradycardia Due to Drug Interactions [see Warnings and Precautions (5.5)]
- Allergic-Type Reactions [see Warnings and Precautions (5.6)]
- Systemic Toxicities with Unintended Intravascular or Intrathecal Injection [see Warnings and Precautions (5.7)]
- Respiratory Arrest Following Retrobulbar Block [see Warnings and Precautions (5.14)]

The following adverse reactions from voluntary reports or clinical studies have been reported with lidocaine or lidocaine and epinephrine. Because many of these reactions were reported voluntarily from a population of uncertain size, it is not always possible to reliably estimate their frequency or establish a causal relationship to drug exposure.

Adverse reactions to Lidocaine Hydrochloride Injection are characteristic of those associated with other amide‑type local anesthetics. A major cause of adverse reactions to this group of drugs is excessive plasma levels, which may be due to overdosage, unintentional intravascular injection, or slow metabolic degradation.

The most commonly encountered acute adverse reactions that demand immediate counter measures were related to the CNS and the cardiovascular system. These adverse reactions were generally dose-related and due to high plasma levels which may have resulted from overdosage, rapid absorption from the injection site, diminished tolerance, or from unintentional intravascular injection of the local anesthetic solution. In addition to systemic dose-related toxicity, unintentional intrathecal injection of drug during the intended performance of caudal or lumbar epidural block or nerve blocks near the vertebral column (especially in the head and neck region) has resulted in underventilation or apnea (“Total or High Spinal”). Also, hypertension due to loss of sympathetic tone and respiratory paralysis or underventilation due to cephalad extension of the motor level of anesthesia have occurred. This has led to secondary cardiac arrest when untreated.

When used for dental injections, paresthesia of the lips, tongue, and oral tissues have been reported. Persistent paresthesia lasting weeks to months and, in some instances, lasting greater than one year, have also been reported.

Nervous System Disorders

Adverse reactions were characterized by excitation and/or depression of the central nervous system and included lightheadedness, nervousness, apprehension, euphoria, confusion, dizziness, drowsiness, tinnitus, blurred or double vision, vomiting, sensations of heat, cold or numbness, twitching, tremors, convulsions, unconsciousness, respiratory depression and arrest.

The incidences of adverse reactions associated with the use of local anesthetics may be related to the total dose of local anesthetic administered and are also dependent upon the particular drug used, the route of administration and the physical status of the patient. In a prospective review of 10,440 patients who received lidocaine hydrochloride for spinal anesthesia, the incidences of adverse reactions were reported to be about 3 percent each for positional headaches, hypotension and backache; 2 percent for shivering; and less than 1 percent each for peripheral nerve symptoms, nausea, respiratory inadequacy and double vision.

Persistent motor, sensory and/or autonomic (sphincter control) deficit of some lower spinal segments with slow recovery (several months) or incomplete recovery have been reported in rare instances when caudal or lumbar epidural block has been attempted. Backache and headache have also been noted following use of these anesthetic procedures.

There have been reported cases of permanent injury to extraocular muscles requiring surgical repair following retrobulbar administration.

In the practice of caudal or lumbar epidural block, unintentional penetration of the subarachnoid space by the catheter or needle has occurred. Subsequent adverse effects may have depended partially on the amount of drug administered intrathecally and the physiological and physical effects of a dural puncture. A high spinal has been characterized by paralysis of the legs, loss of consciousness, respiratory paralysis, and bradycardia.

Neurologic effects following epidural or caudal anesthesia have included spinal block of varying magnitude (including high or total spinal block); hypotension secondary to spinal block; urinary retention; fecal and urinary incontinence; loss of perineal sensation and sexual function; persistent anesthesia, paresthesia, weakness, paralysis of the lower extremities and loss of sphincter control, all of which had slow, incomplete, or no recovery; headache; backache; septic meningitis; meningismus; slowing of labor; increased incidence of forceps delivery; and cranial nerve palsies due to traction on nerves from loss of cerebrospinal fluid.

Neurologic effects following other procedures or routes of administration have included persistent anesthesia, paresthesia, weakness, paralysis, all with slow, incomplete, or no recovery.

Convulsions: Incidence varied with the procedure used and the total dose administered. In a survey of studies of epidural anesthesia, overt toxicity progressing to convulsions occurred in approximately 0.1% of local anesthetic administrations. The incidences of adverse neurologic reactions associated with the use of local anesthetics may be related to the total dose of local anesthetic administered and are also dependent upon the particular drug used, the route of administration, and the physical status of the patient.

Cardiac Disorders

High doses or unintentional intravascular injection have led to high plasma levels and related depression of the myocardium, decreased cardiac output, heartblock, hypotension, bradycardia, ventricular arrhythmias, including ventricular tachycardia and ventricular fibrillation, and cardiac arrest [see Warnings and Precautions (5.9)].

Immune System Disorders

Allergic reactions are characterized by cutaneous lesions, urticaria, edema or anaphylactoid reactions. Allergic reactions may occur as a result of sensitivity either to local anesthetic agents or to the methylparaben used as a preservative in the multiple‑dose vials [see Warnings and Precautions (5.6)].

There have been no reports of cross sensitivity between lidocaine hydrochloride and procainamide or between lidocaine hydrochloride and quinidine.

Hematologic

Methemoglobinemia [See Warnings and Precautions (5.2)].

7 DRUG INTERACTIONS

7.1 Local Anesthetics

The toxic effects of local anesthetics are additive. If coadministration of other local anesthetics with Lidocaine Hydrochloride Injection cannot be avoided, monitor patients for neurologic and cardiovascular effects related to local anesthetic systemic toxicity [see Warnings and Precautions (5.1)].

7.2 Monoamine Oxidase Inhibitors and Tricyclic Antidepressants

The administration of lidocaine solutions containing epinephrine to patients receiving monoamine oxidase inhibitors or tricyclic antidepressants may produce severe, prolonged hypertension. Concurrent use of these agents should generally be avoided. In situations when concurrent therapy is necessary, careful monitoring of the patient’s hemodynamic status is essential [see Warnings and Precautions (5.5)].

7.3 Ergot-Type Oxytocic Drugs

Concurrent administration of vasopressor drugs (for the treatment of hypotension related to obstetric blocks) and ergot-type oxytocic drugs may cause severe, persistent hypertension or cerebrovascular accidents. Avoid use of lidocaine solutions containing epinephrine concomitantly with ergot-type oxytocic drugs [see Warnings and Precautions (5.5)].

7.4 Nonselective Beta-Adrenergic Antagonists

Administration of lidocaine solutions containing epinephrine in patients receiving nonselective beta-adrenergic antagonists may cause severe hypertension and bradycardia. Concurrent use of these agents should generally be avoided. In situations when concurrent therapy is necessary, careful monitoring of the patient's blood pressure and heart rate is essential [see Warnings and Precautions (5.5)].

7.5 Drugs Associated with Methemoglobinemia

Patients that are administered local anesthetics may be at increased risk of developing methemoglobinemia when concurrently exposed to the following oxidizing agents:

Class | Examples
Nitrates/Nitrites | nitroglycerin, nitroprusside, nitric oxide, nitrous oxide
Local anesthetics | articaine, benzocaine, bupivacaine, lidocaine, mepivacaine, prilocaine, procaine, ropivacaine, tetracaine
Antineoplastic agents | cyclophosphamide, flutamide, rasburicase, ifosfamide, hydroxyurea
Antibiotics | dapsone, sulfonamides, nitrofurantoin, para‑aminosalicylic acid
Antimalarials | chloroquine, primaquine
Anticonvulsants | phenytoin, sodium valproate, phenobarbital
Other drugs | acetaminophen, metoclopramide, quinine, sulfasalazine

7.6 Potent Inhalation Anesthetics

Serious dose-related cardiac arrhythmias may occur if lidocaine solutions containing epinephrine are used in patients during or following the administration of potent inhalation anesthetics [see Warnings and Precautions (5.11)].

8 USE IN SPECIFIC POPULATIONS

8.1 Pregnancy

Risk Summary

Available published data and decades of clinical use with lidocaine hydrochloride in pregnant women have not identified any drug-associated risk for major birth defects, miscarriage, or other adverse maternal or fetal outcomes. Local anesthetics may cause varying degrees of toxicity to the mother and fetus and adverse reactions include alterations of the central nervous system, peripheral vascular tone and cardiac function (see Clinical Considerations).

In a published animal reproduction study, pregnant rats administered lidocaine by continuous subcutaneous infusion at a dose approximately 9.6 times the maximum recommended human dose (MRHD) of 500 mg of lidocaine hydrochloride during the period of organogenesis resulted in lower fetal body weights [see Data].

The estimated background risk of major birth defects and miscarriage for the indicated population is unknown. All pregnancies have a background risk of birth defects, loss, or other adverse outcomes. In the United States general population, the estimated background risks of major birth defects and miscarriage in clinically recognized pregnancies is 2% to 4% and 15% to 20%, respectively.

Clinical Considerations

Maternal Adverse Reactions

Maternal hypotension has resulted from regional anesthesia. Local anesthetics produce vasodilation by blocking sympathetic nerves. Therefore, during treatment of systemic toxicity, maternal hypotension or fetal bradycardia following regional block, the parturient should be maintained in the left lateral decubitus position if possible or manual displacement of the uterus off the great vessels be accomplished. Elevating the patient’s legs will also help prevent decreases in blood pressure. The fetal heart rate also should be monitored continuously, and electronic fetal monitoring is highly advisable.

Labor or Delivery

Local anesthetics rapidly cross the placenta, and when used for epidural, paracervical, pudendal or caudal block anesthesia, can cause varying degrees of maternal, fetal and neonatal toxicity [see Clinical Pharmacology (12.3)]. The incidence and degree of toxicity depend upon the procedure performed, the type and amount of drug used, and the technique of drug administration. Adverse reactions in the parturient, fetus and neonate involve alterations of the central nervous system, peripheral vascular tone and cardiac function. However, dosage recommendations for spinal anesthesia are much lower than dosage recommendations for other major blocks.

Spinal anesthesia may alter the forces of parturition through changes in uterine contractility or maternal expulsive efforts. Spinal anesthesia has also been reported to prolong the second stage of labor by removing the parturient’s reflex urge to bear down or by interfering with motor function. The use of obstetrical anesthesia may increase the need for forceps assistance. The use of some local anesthetic drug products during labor and delivery may be followed by diminished muscle strength and tone for the first day or two of life.

Data

Animal Data

Reproduction studies have been performed in rats at doses up to 6.6 times the human dose and have revealed no evidence of harm to the fetus caused by lidocaine hydrochloride.

In a published study, lidocaine administered to pregnant rats by continuous subcutaneous infusion during the period of organogenesis at 100, 250, and 500 mg/kg/day, did not produce any structural abnormalities, but did result in lower fetal weights at 500 mg/kg/day dose (approximately 9.6 times the maximum recommended human dose [MRHD] of 500 mg lidocaine on a mg/m^2 basis) in the absence of maternal toxicity.

8.2 Lactation

Risk Summary

Published data report the presence of lidocaine and its metabolites in human milk in low amounts, along with poor oral bioavailability. There are no data on the effect of lidocaine on the breastfed infant or the effect on milk production. The developmental and health benefits of breastfeeding should be considered along with the mother’s clinical need for Lidocaine Hydrochloride Injection and any potential adverse effects on the breastfed child from Lidocaine Hydrochloride Injection or from the underlying maternal condition.

8.4 Pediatric Use

Dosages in children should be reduced, commensurate with age, body weight and physical condition [see Dosage and Administration (2.6)].

8.5 Geriatric Use

Elderly patients should be given reduced doses commensurate with their age and physical condition [see Dosage and Administration (2.6)].

8.6 Hepatic Impairment

Amide-type local anesthetics such as lidocaine are metabolized by the liver. Patients with severe hepatic impairment, because of their inability to metabolize local anesthetics normally, are at greater risk of developing toxic plasma concentrations and potentially local anesthetic systemic toxicity. Therefore, consider reduced dosing and increased monitoring for local anesthetic systemic toxicity in patients with hepatic impairment treated with Lidocaine Hydrochloride Injection, especially with repeat doses [see Warnings and Precautions (5.8)].

10 OVERDOSAGE

Clinical Presentation

Acute emergencies from local anesthetics are generally related to high plasma levels encountered during therapeutic use of local anesthetics or to unintended subarachnoid injection of local anesthetic solution [see Warnings and Precautions (5.1), Adverse Reactions (6)].

Management

The first consideration is prevention, best accomplished by careful and constant monitoring of cardiovascular and respiratory vital signs and the patient’s state of consciousness after each local anesthetic injection. At the first sign of change, oxygen should be administered.

The first step in the management of convulsions, as well as underventilation or apnea due to unintended subarachnoid injection of drug solution, consists of immediate attention to the maintenance of a patent airway and assisted or controlled ventilation with oxygen and a delivery system capable of permitting immediate positive airway pressure by mask. Immediately after the institution of these ventilatory measures, the adequacy of the circulation should be evaluated, keeping in mind that drugs used to treat convulsions sometimes depress the circulation when administered intravenously. Should convulsions persist despite adequate respiratory support, and if the status of the circulation permits, a benzodiazepine (such as diazepam) may be administered intravenously. The clinician should be familiar, prior to the use of local anesthetics, with these anticonvulsant drugs. Supportive treatment of circulatory depression may require administration of intravenous fluids and, when appropriate, a vasopressor as directed by the clinical situation (e.g., ephedrine).

If not treated immediately, both convulsions and cardiovascular depression can result in hypoxia, acidosis, bradycardia, arrhythmias and cardiac arrest. Underventilation or apnea due to unintentional subarachnoid injection of local anesthetic solution may produce these same signs and also lead to cardiac arrest if ventilatory support is not instituted. If cardiac arrest should occur, standard cardiopulmonary resuscitative measures should be instituted.

Endotracheal intubation, employing drugs and techniques familiar to the clinician, may be indicated, after initial administration of oxygen by mask, if difficulty is encountered in the maintenance of a patent airway or if prolonged ventilatory support (assisted or controlled) is indicated.

Dialysis is of negligible value in the treatment of acute overdosage with lidocaine hydrochloride.

11 DESCRIPTION

Lidocaine Hydrochloride Injection, USP contains lidocaine hydrochloride, an amide local anesthetic, as the active pharmaceutical ingredient. The route of administration for Lidocaine Hydrochloride Injection is by injection, for infiltration, nerve block, epidural and caudal use. Multiple‑dose vials contain methylparaben and they should not be used for caudal and lumbar epidural blocks.

Lidocaine hydrochloride is chemically designated as acetamide, 2-(diethylamino)-N-(2,6-dimethylphenyl), monohydrochloride monohydrate and has the molecular weight is of 288.8 g/mol. Lidocaine hydrochloride molecular formula is C14H22N2O•HCl•H2O, and has the following structural formula:

Lidocaine Hydrochloride Injection, USP is a sterile, nonpyrogenic, isotonic, clear solution containing lidocaine hydrochloride and sodium chloride in water for injection for parenteral administration in various concentrations with characteristics as follows:

Concentration | 0.5% | 1% | 1.5% | 2%
mg/mL lidocaine hydrochloride; (anhydrous) | 5 | 10 | 15 | 20
mg/mL sodium chloride | 8 | 7 | 6.5 | 6

Multiple-dose vials contain 0.1% of methylparaben added as an antiseptic preservative. May contain sodium hydroxide and/or hydrochloric acid for pH adjustment. The pH is 6.5 (5.0 to 7.0) [See How Supplied/Storage and Handling (16)] for various sizes and strengths.

The semi-rigid vial used for the plastic vials is fabricated from a specially formulated polyolefin. It is a copolymer of ethylene and propylene. The safety of the plastic has been confirmed by tests in animals according to USP biological standards for plastic containers. The container requires no vapor barrier to maintain the proper drug concentration.

12 CLINICAL PHARMACOLOGY

12.1 Mechanism of Action

Lidocaine hydrochloride stabilizes the neuronal membrane by inhibiting the ionic fluxes required for the initiation and conduction of impulses thereby effecting local anesthetic action.

12.2 Pharmacodynamics

Excessive blood levels may cause changes in cardiac output, total peripheral resistance, and mean arterial pressure. With central neural blockade these changes may be attributable to block of autonomic fibers, a direct depressant effect of the local anesthetic agent on various components of the cardiovascular system, and/or the beta-adrenergic receptor stimulating action of epinephrine when present. The net effect is normally a modest hypotension when the recommended dosages are not exceeded.

Factors such as acidosis and the use of CNS stimulants and depressants affect the CNS levels of lidocaine hydrochloride required to produce overt systemic effects. Objective adverse manifestations become increasingly apparent with increasing venous plasma levels above 6 mcg free base per mL.

12.3 Pharmacokinetics

Systemic plasma levels of lidocaine following Lidocaine Hydrochloride Injection do not correlate with local efficacy.

Absorption

Information derived from diverse formulations, concentrations and usages reveals that lidocaine hydrochloride is completely absorbed following parenteral administration, its rate of absorption depending, for example, upon various factors such as the site of administration and the presence or absence of a vasoconstrictor agent. Except for intravascular administration, the highest blood levels are obtained following intercostal nerve block and the lowest after subcutaneous administration.

Distribution

The plasma binding of lidocaine hydrochloride is dependent on drug concentration, and the fraction bound decreases with increasing concentration. At concentrations of 1 to 4 mcg of free base per mL 60 to 80 percent of lidocaine hydrochloride is protein bound. Binding is also dependent on the plasma concentration of the alpha-1‑acid glycoprotein.

Lidocaine hydrochloride crosses the blood-brain and placental barriers, presumably by passive diffusion.

Elimination

The elimination half-life of lidocaine hydrochloride following an intravenous bolus injection is typically 1.5 to 2 hours.

Metabolism

Lidocaine hydrochloride is metabolized rapidly by the liver, and biotransformation includes oxidative N‑dealkylation, ring hydroxylation, cleavage of the amide linkage, and conjugation. N-dealkylation, a major pathway of biotransformation, yields the metabolites monoethylglycinexylidide and glycinexylidide. The pharmacological/toxicological actions of these metabolites are similar to, but less potent than, those of lidocaine hydrochloride.

Excretion

Approximately 90% of lidocaine hydrochloride administered is excreted in the form of various metabolites, and less than 10% is excreted unchanged by the kidneys. The primary metabolite in urine is a conjugate of 4‑hydroxy-2,6-dimethylaniline.

Specific Populations

Patients with Hepatic Impairment

Because of the rapid rate at which lidocaine hydrochloride is metabolized, any condition that affects liver function may alter lidocaine hydrochloride kinetics. The half-life may be prolonged two-fold or more in patients with liver dysfunction.

Patients with Renal Impairment

Renal dysfunction does not affect lidocaine hydrochloride kinetics but may increase the accumulation of metabolites.

13 NONCLINICAL TOXICOLOGY

13.1 Carcinogenesis, Mutagenesis, Impairment of Fertility

Carcinogenesis

Studies of lidocaine hydrochloride in animals to evaluate the carcinogenic potential have not been conducted.

Mutagenesis

Studies of lidocaine hydrochloride in animals to evaluate the mutagenic potential have not been conducted.

Impairment of Fertility

In a published study, female Sprague-Dawley rats were treated subcutaneously with lidocaine via osmotic pumps starting two weeks prior to mating, and reproductive effects were assessed. Rats dosed up to the high dose of 500 mg/kg/day (approximately 45 times the MRDD on a mg/m^2 basis) showed no effects on copulatory rate, pregnancy rate, numbers of corpora lutea, or implantations.

16 HOW SUPPLIED/STORAGE AND HANDLING

Store at 20°C to 25°C (68°F to 77°F). [see USP Controlled Room Temperature.]

Lidocaine Hydrochloride Injection, USP solutions packaged in ampuls and glass teartop vials may be autoclaved one time only. Autoclave at 15 pounds pressure, 121°C (250°F) for 15 minutes. DO NOT AUTOCLAVE PRODUCT IN PLASTIC VIALS.

For single-dose vials and ampuls: Discard unused portion.

Single-dose products are preservative-free.

Lidocaine Hydrochloride Injection, USP is supplied as follows. This product is a clear solution.

Unit of Sale | Concentration
Overbagged with 5 x 20mL Plastic Multiple-dose Fliptop Vials in each bag, NDC 55154-0124-5 | 1% 200 mg/20 mL (10 mg/mL)

WARNING: This Unit Dose package is not child resistant and is Intended for Institutional Use Only. Keep this and all drugs out of the reach of children.

17 PATIENT COUNSELING INFORMATION

17.1 Allergic-Type Reactions

Assess if the patient has had allergic-type reactions to amide-type local anesthetics or to other formulation ingredients, such as the antimicrobial preservative methylparaben contained in multiple-dose vials [see Contraindications (4), Warnings and Precautions (5.6), Adverse Reactions (6)].

17.2 Temporary Loss of Sensation and Motor Activity After Caudal or Epidural Anesthesia

When appropriate, patients should be informed in advance that they may experience temporary loss of sensation and motor activity, usually in the lower half of the body, following proper administration of caudal or epidural anesthesia.

Instructions After Dental Injection of Lidocaine Hydrochloride Injection

Advise patients receiving dental injections of Lidocaine Hydrochloride Injection not to chew solid foods or to test the anesthetized area by biting or probing until anesthesia has worn off (up to 7 hours) [see Warnings and Precautions (5.15)].

17.3 Methemoglobinemia

Inform patients that use of local anesthetics may cause methemoglobinemia, a serious condition that must be treated promptly. Advise patients or caregivers to stop use and seek immediate medical attention if they or someone in their care experience the following signs or symptoms: pale, gray, or blue colored skin (cyanosis); headache; rapid heart rate; shortness of breath; lightheadedness; or fatigue [see Warnings and Precautions (5.2)].

This product’s labeling may have been updated. For the most recent prescribing information, please visit www.pfizer.com.

Distributed by Hospira, Inc., Lake Forest, IL 60045 USA

Distributed By:

Cardinal Health

Dublin, OH 43017

L28635381125

LAB-1118-6.0

Package/Label Display Panel

NDC 55154-0124-5

LIDOCAINE HCl INJECTION, USP

1% 200 mg/20 mL (10 mg/mL)

5 x 20 mL MULTIPLE-DOSE FLIPTOP VIALS